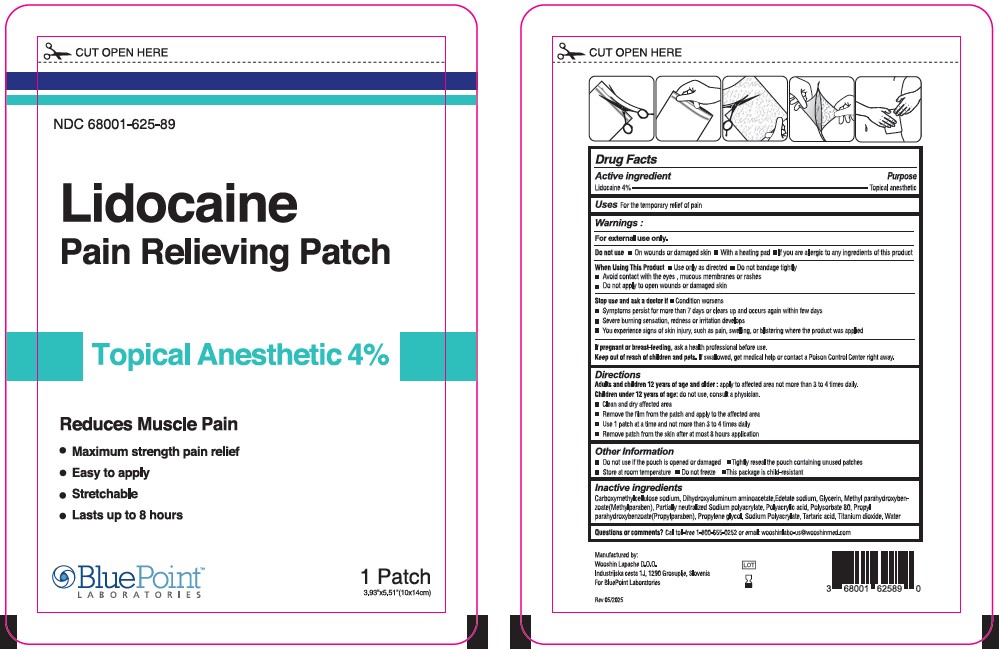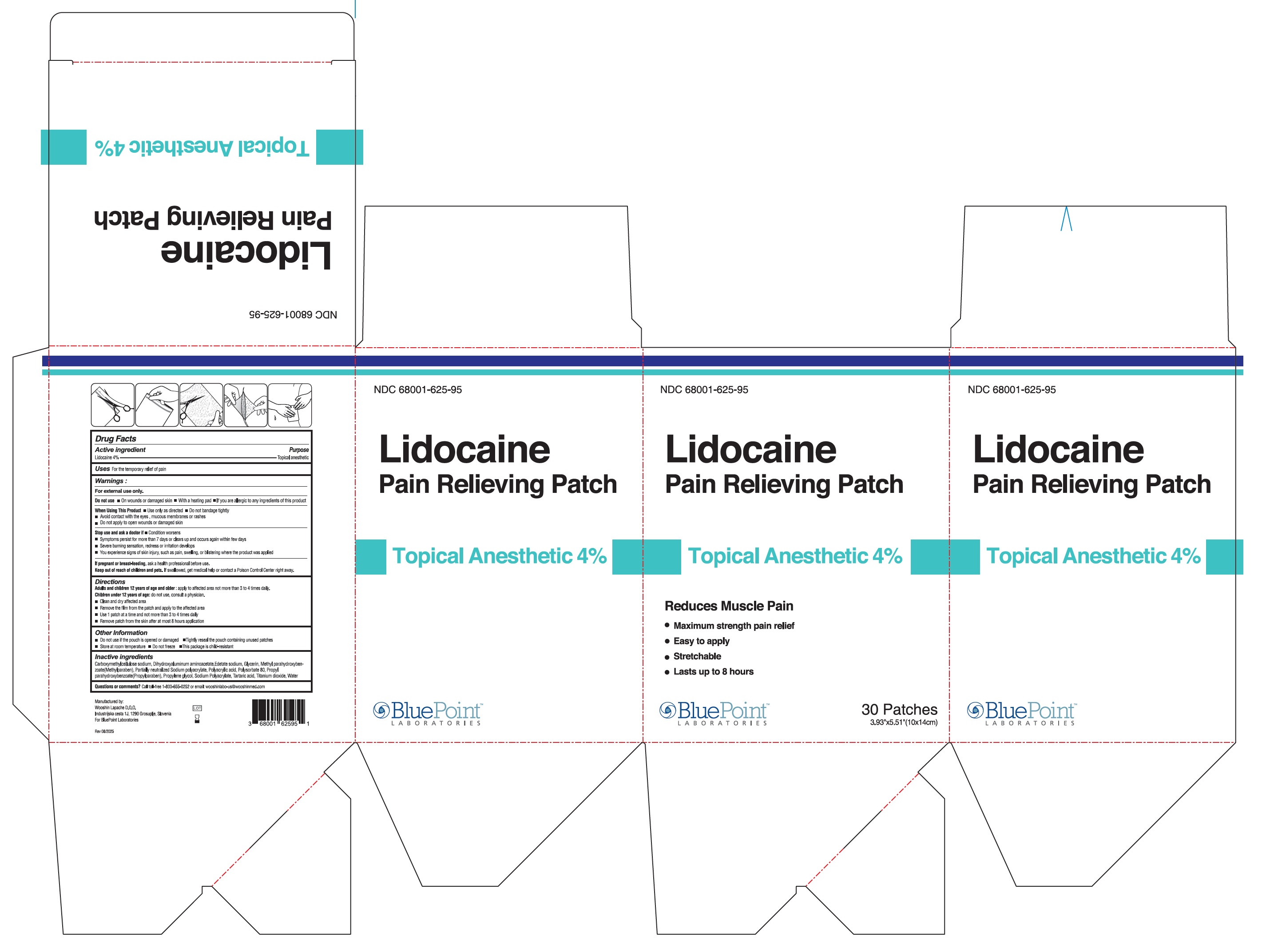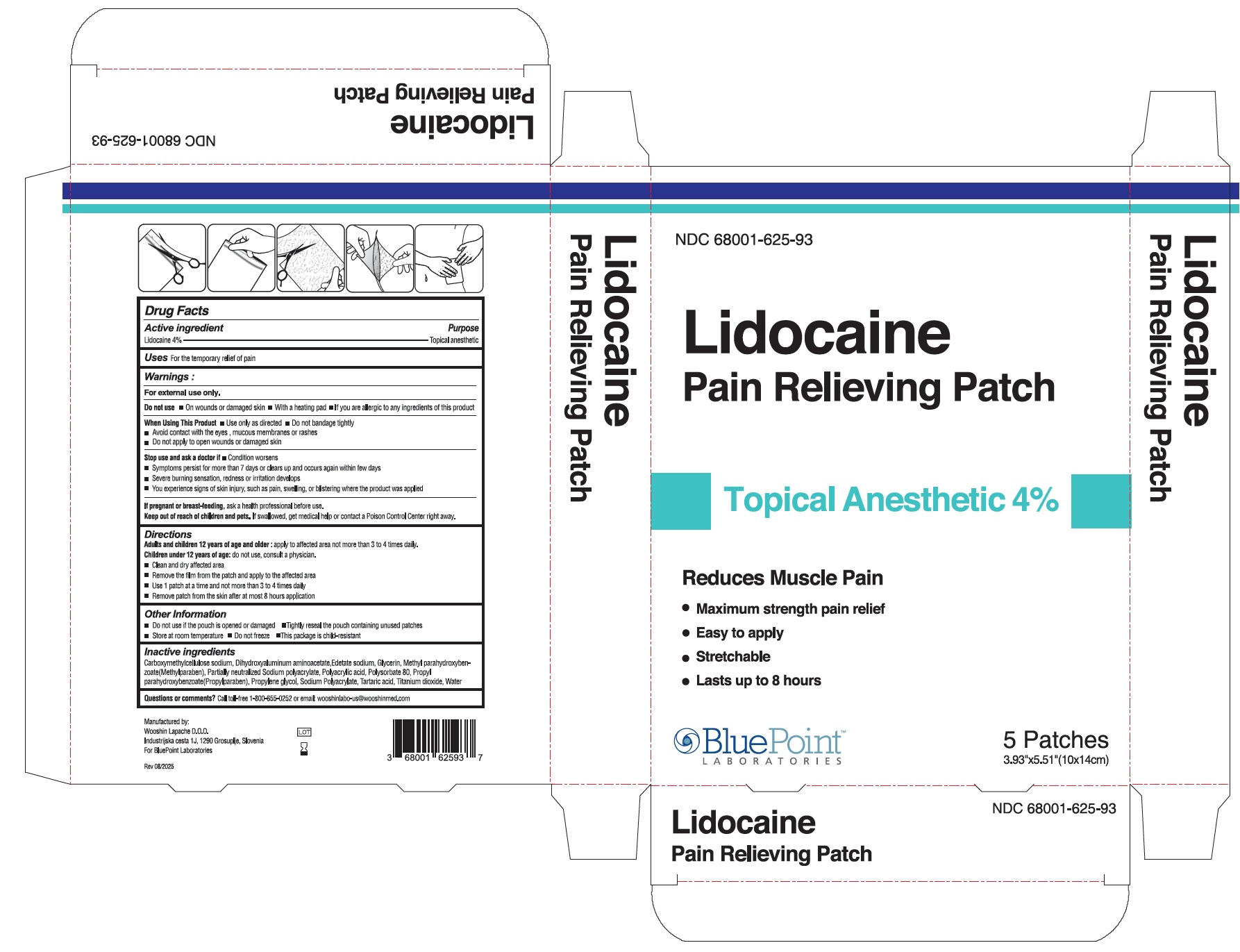 DRUG LABEL: Lidocaine Pain Relieving Patch
NDC: 68001-625 | Form: PATCH
Manufacturer: BluePoint Laboratories
Category: otc | Type: HUMAN OTC DRUG LABEL
Date: 20251008

ACTIVE INGREDIENTS: LIDOCAINE 40 mg/1 g
INACTIVE INGREDIENTS: TARTARIC ACID; POLYSORBATE 80; POLYACRYLIC ACID (250000 MW); SODIUM POLYACRYLATE (2500000 MW); TITANIUM DIOXIDE; DIHYDROXYALUMINUM AMINOACETATE ANHYDROUS; METHYLPARABEN; EDETATE SODIUM; PROPYLPARABEN; WATER; GLYCERIN; CARBOXYMETHYLCELLULOSE SODIUM, UNSPECIFIED FORM; PROPYLENE GLYCOL

Lidocaine Pain Relieving Patch - Lidocaine 4%

Active ingredient

Lidocaine 4%

Purpose

Topical anesthetic

Uses

For the temporary relief of pain

Warnings:

For external use only.

Do not Use

- On wounds or damaged skin
- With a heating pad
- If you are allergic to any ingredients of this product

When Using This Product

- Use only as directed
- Do not bandage tightly
- Avoid contact with the eyes, mucous membranes or rashes
- Do not apply to open wounds or damaged skin

Stop Use and Ask a Doctor if

- Condition worsens
- Symptoms persist for more than 7 days or clears up and occurs again within a few days
- Severe burning sensation, redness or irritation develops
- You experience signs of skin injury, such as pain, swelling, or blistering where the product was applied

PREGNANCY OR BREAST FEEDING

If pregnant or breast-feeding, ask a health professional before use.

Keep Out of Reach of Children and Pets. If swallowed, get medical help or contact a Poison Control Center right away.

Directions:

Adults and children 12 years of age and older: apply to affected area not more than 3 to 4 times daily.

Children under 12 years of age: do not use, consult a physician.

- Clean and dry affected area
- Remove the film from the patch and apply to the affected area
- Use 1 patch at a time and not more than 3 to 4 times daily
- Remove patch from the skin after at most 8 hours application

Other information

- Do not use if the pouch is opened or damaged
- Tighlty reseal the pouch containing unused patches
- Store at room temperature
- Do not freeze
- This package is child-resistant

Inactive ingredients

Carboxymethylcellulose sodium, Dihydroxyaluminum aminoacetate, Edetate sodium, Glycerin, Methyl parahydroxybenzoate (Methylparaben), Partially neutralized Sodium Polyacrylate, Polyacrylic acid, Polysorbate 80, Propyl parahydroxybenzoate (Propylparaben), Propylene glycol, Sodium Polyacrylate, Tartaric acid, Titanium dioxide, Water.

Questions or comments?

Call toll-free 1-800-655-0252 or email: wooshinlabo-us@wooshinmed.com

Principal Display Panel

Lidocaine Pain Relieving Patch Pouch 4%

NDC 68001-625-89

Rev 05/25

Lidocaine Pain Relieving Patch 5 Patch Carton 4%

NDC 68001-625-93

Rev 08/25

Lidocaine Pain Relieving Patch 30 Patch Carton 4%

NDC 68001-625-95

Rev 08/25